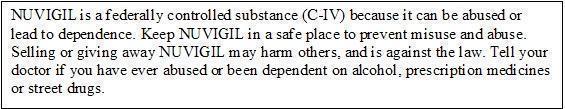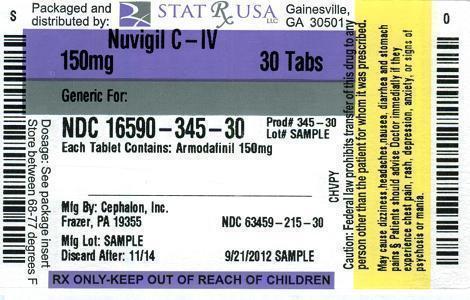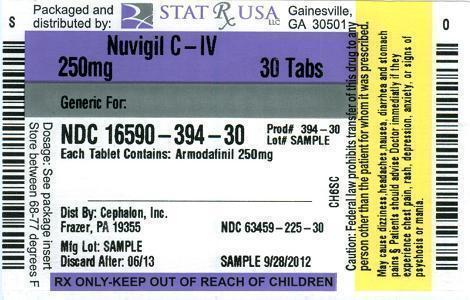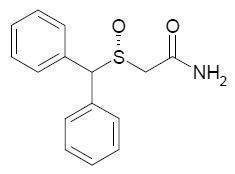 DRUG LABEL: NUVIGIL
NDC: 16590-345 | Form: TABLET
Manufacturer: STAT Rx USA LLC
Category: prescription | Type: HUMAN PRESCRIPTION DRUG LABEL
Date: 20121008
DEA Schedule: CIV

ACTIVE INGREDIENTS: ARMODAFINIL 150 mg/1 1
INACTIVE INGREDIENTS: CROSCARMELLOSE SODIUM; LACTOSE MONOHYDRATE; MAGNESIUM STEARATE; CELLULOSE, MICROCRYSTALLINE; POVIDONE; STARCH, CORN

NUVIGIL® (armodafinil) Tablets [C-IV]

DESCRIPTION

NUVIGIL® (armodafinil) is a wakefulness-promoting agent for oral administration. Armodafinil is the R-enantiomer of modafinil which is a mixture of the R- and S-enantiomers. The chemical name for armodafinil is 2-[(R)-(diphenylmethyl)sulfinyl]acetamide. The molecular formula is C15H15NO2S and the molecular weight is 273.35.

The chemical structure is:

Armodafinil exists in multiple crystalline forms. Form I, which is used in NUVIGIL, is the least soluble form of armodafinil and is a white to off-white, crystalline powder that is very slightly soluble in water, sparingly soluble in acetone and soluble in methanol. At least 90% of the armodafinil particles used in NUVIGIL have a diameter less than 200 microns.

NUVIGIL tablets contain 50, 150, or 250 mg of armodafinil and the following inactive ingredients: croscarmellose sodium, lactose monohydrate, magnesium stearate, microcrystalline cellulose, povidone, and pregelatinized starch.

CLINICAL PHARMACOLOGY

Mechanism of Action and Pharmacology

The precise mechanism(s) through which armodafinil (R-enantiomer) or modafinil (mixture of R- and S-enantiomers) promote wakefulness is unknown. Both armodafinil and modafinil have shown similar pharmacological properties in nonclinical animal and in vitro studies, to the extent tested.

At pharmacologically relevant concentrations, armodafinil does not bind to or inhibit several receptors and enzymes potentially relevant for sleep/wake regulation, including those for serotonin, dopamine, adenosine, galanin, melatonin, melanocortin, orexin-1, orphanin, PACAP or benzodiazepines, or transporters for GABA, serotonin, norepinephrine, and choline or phosphodiesterase VI, COMT, GABA transaminase, and tyrosine hydroxylase. Modafinil does not inhibit the activity of MAO-B or phosphodiesterases II-IV.

Modafinil-induced wakefulness can be attenuated by the α1-adrenergic receptor antagonist, prazosin; however, modafinil is inactive in other in vitro assay systems known to be responsive to α-adrenergic agonists such as the rat vas deferens preparation.

Armodafinil is not a direct- or indirect-acting dopamine receptor agonist. However, in vitro, both armodafinil and modafinil bind to the dopamine transporter and inhibit dopamine reuptake. For modafinil, this activity has been associated in vivo with increased extracellular dopamine levels in some brain regions of animals. In genetically engineered mice lacking the dopamine transporter (DAT), modafinil lacked wake-promoting activity, suggesting that this activity was DAT-dependent. However, the wake-promoting effects of modafinil, unlike those of amphetamine, were not antagonized by the dopamine receptor antagonist haloperidol in rats. In addition, alpha-methyl-p-tyrosine, a dopamine synthesis inhibitor, blocks the action of amphetamine, but does not block locomotor activity induced by modafinil.

Armodafinil and modafinil have wake-promoting actions similar to sympathomimetic agents including amphetamine and methylphenidate, although their pharmacologic profile is not identical to that of the sympathomimetic amines. In addition to its wake-promoting effects and ability to increase locomotor activity in animals, modafinil produces psychoactive and euphoric effects, alterations in mood, perception, thinking, and feelings typical of other CNS stimulants in humans. Modafinil has reinforcing properties, as evidenced by its self-administration in monkeys previously trained to self-administer cocaine; modafinil was also partially discriminated as stimulant-like.

Based on nonclinical studies, two major metabolites, acid and sulfone, of modafinil or armodafinil, do not appear to contribute to the CNS-activating properties of the parent compounds.

Pharmacokinetics

The active component of NUVIGIL is armodafinil, which is the longer-lived enantiomer of modafinil. NUVIGIL exhibits linear time-independent kinetics following single and multiple oral dose administration. Increase in systemic exposure is proportional over the dose range of 50 to 400 mg. No time-dependent change in kinetics was observed through 12 weeks of dosing. Apparent steady state for NUVIGIL was reached within 7 days of dosing. At steady state, the systemic exposure for NUVIGIL is 1.8 times the exposure observed after a single dose. The concentration-time profiles of the pure R-enantiomer following administration of 50 mg NUVIGIL or 100 mg PROVIGIL® (modafinil) are nearly superimposable.

Absorption

NUVIGIL is readily absorbed after oral administration. The absolute oral bioavailability was not determined due to the aqueous insolubility of armodafinil, which precluded intravenous administration. Peak plasma concentrations are attained at approximately 2 hours in the fasted state. Food effect on the overall bioavailability of NUVIGIL is considered minimal; however, time to reach peak concentration (tmax) may be delayed by approximately 2-4 hours in the fed state. Since the delay in tmax is also associated with elevated plasma levels later in time, food can potentially affect the onset and time course of pharmacologic action for NUVIGIL.

Distribution

NUVIGIL has an apparent volume of distribution of approximately 42 L. Data specific to armodafinil protein binding are not available. However, modafinil is moderately bound to plasma protein (approximately 60%), mainly to albumin. The potential for interactions of NUVIGIL with highly protein-bound drugs is considered to be minimal.

Metabolism

In vitro and in vivo data show that armodafinil undergoes hydrolytic deamidation, S-oxidation, and aromatic ring hydroxylation, with subsequent glucuronide conjugation of the hydroxylated products. Amide hydrolysis is the single most prominent metabolic pathway, with sulfone formation by cytochrome P450 (CYP) 3A4/5 being next in importance. The other oxidative products are formed too slowly in vitro to enable identification of the enzyme(s) responsible. Only two metabolites reach appreciable concentrations in plasma (i.e., R-modafinil acid and modafinil sulfone).

Data specific to NUVIGIL disposition are not available. However, modafinil is mainly eliminated via metabolism, predominantly in the liver, with less than 10% of the parent compound excreted in the urine. A total of 81% of the administered radioactivity was recovered in 11 days post-dose, predominantly in the urine (80% vs. 1.0% in the feces).

Elimination

After oral administration of NUVIGIL, armodafinil exhibits an apparent monoexponential decline from the peak plasma concentration. The apparent terminal t½ is approximately 15 hours. The oral clearance of NUVIGIL is approximately 33 mL/min.

Drug-Drug Interactions

The existence of multiple pathways for armodafinil metabolism, as well as the fact that a non-CYP-related pathway is the most rapid in metabolizing armodafinil, suggest that there is a low probability of substantive effects on the overall pharmacokinetic profile of NUVIGIL due to CYP inhibition by concomitant medications.

In vitro data demonstrated that armodafinil shows a weak inductive response for CYP1A2 and possibly CYP3A activities in a concentration-related manner and that CYP2C19 activity is reversibly inhibited by armodafinil. Other CYP activities did not appear to be affected by armodafinil. An in vitro study demonstrated that armodafinil is a substrate of P-glycoprotein.

Chronic administration of NUVIGIL at 250 mg reduced the systemic exposure to midazolam by 32% and 17% after single oral (5 mg) and intravenous (2 mg) doses, respectively, suggesting that administration of NUVIGIL moderately induces CYP3A activity. Drugs that are substrates for CYP3A4/5, such as cyclosporine, may require dosage adjustment. (SeePRECAUTIONS, Drug Interactions).

Chronic administration of NUVIGIL at 250 mg did not affect the pharmacokinetics of caffeine (200 mg), a probe substrate for CYP1A2 activity.

Coadministration of a single 400-mg dose of NUVIGIL with omeprazole (40 mg) increased systemic exposure to omeprazole by approximately 40%, indicating that armodafinil moderately inhibits CYP2C19 activity. Drugs that are substrates for CYP2C19 may require dosage reduction. (SeePRECAUTIONS, Drug Interactions).

Gender Effect

Population pharmacokinetic analysis suggests no gender effect on the pharmacokinetics of armodafinil.

Special Populations

Data specific to armodafinil in special populations are not available.

Age Effect:

A slight decrease (~20%) in the oral clearance (CL/F) of modafinil was observed in a single dose study at 200 mg in 12 subjects with a mean age of 63 years (range 53 – 72 years), but the change was considered not likely to be clinically significant. In a multiple dose study (300 mg/day) in 12 patients with a mean age of 82 years (range 67 – 87 years), the mean levels of modafinil in plasma were approximately two times those historically obtained in matched younger subjects. Due to potential effects from the multiple concomitant medications with which most of the patients were being treated, the apparent difference in modafinil pharmacokinetics may not be attributable solely to the effects of aging. However, the results suggest that the clearance of modafinil may be reduced in the elderly (SeeDOSAGE AND ADMINISTRATION).

Race Effect:

The influence of race on the pharmacokinetics of modafinil has not been studied.

Renal Impairment:

In a single dose 200 mg modafinil study, severe chronic renal failure (creatinine clearance ≤20 mL/min) did not significantly influence the pharmacokinetics of modafinil, but exposure to modafinil acid was increased 9-fold (SeePRECAUTIONS).

Hepatic Impairment:

The pharmacokinetics and metabolism of modafinil were examined in patients with cirrhosis of the liver (6 men and 3 women). Three patients had stage B or B+ cirrhosis and 6 patients had stage C or C+ cirrhosis (per the Child-Pugh score criteria). Clinically 8 of 9 patients were icteric and all had ascites. In these patients, the oral clearance of modafinil was decreased by about 60% and the steady state concentration was doubled compared to normal patients. The dose of NUVIGIL should be reduced in patients with severe hepatic impairment (SeePRECAUTIONS andDOSAGE AND ADMINISTRATION).

CLINICAL TRIALS

The effectiveness of NUVIGIL in improving wakefulness has been established in the following sleep disorders: obstructive sleep apnea (OSA), narcolepsy and shift work disorder (SWD).

For each clinical trial, a p-value of ≤ 0.05 was required for statistical significance.

Obstructive Sleep Apnea Syndrome (OSA)

The effectiveness of NUVIGIL in improving wakefulness in patients with excessive sleepiness associated with OSA was established in two 12-week, multi-center, placebo-controlled, parallel-group, double-blind studies of outpatients who met the International Classification of Sleep Disorders (ICSD) criteria for OSA (which are also consistent with the American Psychiatric Association DSM-IV criteria). These criteria include either, 1) excessive sleepiness or insomnia, plus frequent episodes of impaired breathing during sleep, and associated features such as loud snoring, morning headaches or dry mouth upon awakening; or 2) excessive sleepiness or insomnia; and polysomnography demonstrating one of the following: more than five obstructive apneas, each greater than 10 seconds in duration, per hour of sleep; and one or more of the following: frequent arousals from sleep associated with the apneas, bradytachycardia, or arterial oxygen desaturation in association with the apneas. In addition, for entry into these studies, all patients were required to have excessive sleepiness as demonstrated by a score ≥ 10 on the Epworth Sleepiness Scale, despite treatment with continuous positive airway pressure (CPAP). Evidence that CPAP was effective in reducing episodes of apnea/hypopnea was required along with documentation of CPAP use.

Patients were required to be compliant with CPAP, defined as CPAP use ≥ 4 hours/night on ≥ 70% of nights. CPAP use continued throughout the study. In both studies, the primary measures of effectiveness were 1) sleep latency, as assessed by the Maintenance of Wakefulness Test (MWT) and 2) the change in the patient’s overall disease status, as measured by the Clinical Global Impression of Change (CGI-C) at the final visit. For a successful trial both measures had to show statistically significant improvement.

The MWT measures latency (in minutes) to sleep onset. An extended MWT was performed with test sessions at 2 hour intervals between 9AM and 7PM. The primary analysis was the average of the sleep latencies from the first four test sessions (9AM to 3PM). For each test session, the subject was asked to attempt to remain awake without using extraordinary measures. Each test session was terminated after 30 minutes if no sleep occurred or immediately after sleep onset. The CGI-C is a 7-point scale, centered at No Change, and ranging from Very Much Worse to Very Much Improved. Evaluators were not given any specific guidance about the criteria they were to apply when rating patients.

In the first study, a total of 395 patients with OSA were randomized to receive NUVIGIL 150 mg/day, NUVIGIL 250 mg/day or matching placebo. Patients treated with NUVIGIL showed a statistically significant improvement in the ability to remain awake compared to placebo-treated patients as measured by the MWT at final visit. A statistically significant greater number of patients treated with NUVIGIL showed improvement in overall clinical condition as rated by the CGI-C scale at final visit. The average sleep latencies (in minutes) in the MWT at baseline for the trials are shown in Table 1 below, along with the average change from baseline on the MWT at final visit. The percentages of patients who showed any degree of improvement on the CGI-C in the clinical trials are shown in Table 2 below. The two doses of NUVIGIL produced statistically significant effects of similar magnitudes on the MWT, and also on the CGI-C.

In the second study, 263 patients with OSA were randomized to either NUVIGIL 150 mg/day or placebo. Patients treated with NUVIGIL showed a statistically significant improvement in the ability to remain awake compared to placebo-treated patients as measured by the MWT [Table 1]. A statistically significant greater number of patients treated with NUVIGIL showed improvement in overall clinical condition as rated by the CGI-C scale [Table 2].

Nighttime sleep measured with polysomnography was not affected by the use of NUVIGIL in either study.

Narcolepsy

The effectiveness of NUVIGIL in improving wakefulness in patients with excessive sleepiness (ES) associated with narcolepsy was established in one 12-week, multi-center, placebo-controlled, parallel-group, double-blind study of outpatients who met the ICSD criteria for narcolepsy. A total of 196 patients were randomized to receive NUVIGIL 150 or 250 mg/day, or matching placebo. The ICSD criteria for narcolepsy include either 1) recurrent daytime naps or lapses into sleep that occur almost daily for at least three months, plus sudden bilateral loss of postural muscle tone in association with intense emotion (cataplexy), or 2) a complaint of excessive sleepiness or sudden muscle weakness with associated features: sleep paralysis, hypnagogic hallucinations, automatic behaviors, disrupted major sleep episode; and polysomnography demonstrating one of the following: sleep latency less than 10 minutes or rapid eye movement (REM) sleep latency less than 20 minutes and a Multiple Sleep Latency Test (MSLT) that demonstrates a mean sleep latency of less than 5 minutes and two or more sleep onset REM periods and no medical or mental disorder accounts for the symptoms. For entry into these studies, all patients were required to have objectively documented excessive daytime sleepiness, via MSLT with a sleep latency of 6 minutes or less and the absence of any other clinically significant active medical or psychiatric disorder. The MSLT, an objective polysomnographic assessment of the patient’s ability to fall asleep in an unstimulating environment, measured latency (in minutes) to sleep onset averaged over 4 test sessions at 2-hour intervals. For each test session, the subject was told to lie quietly and attempt to sleep. Each test session was terminated after 20 minutes if no sleep occurred or immediately after sleep onset.

The primary measures of effectiveness were: 1) sleep latency as assessed by the Maintenance of Wakefulness Test (MWT) and 2) the change in the patient’s overall disease status, as measured by the Clinical Global Impression of Change (CGI-C) at the final visit (See CLINICAL TRIALS, OSA section above for a description of these measures). Each MWT test session was terminated after 20 minutes if no sleep occurred or immediately after sleep onset in this study.

Patients treated with NUVIGIL showed a statistically significantly enhanced ability to remain awake on the MWT at each dose compared to placebo at final visit [Table 1]. A statistically significant greater number of patients treated with NUVIGIL at each dose showed improvement in overall clinical condition as rated by the CGI-C scale at final visit [Table 2].

The two doses of NUVIGIL produced statistically significant effects of similar magnitudes on the CGI-C. Although a statistically significant effect on the MWT was observed for each dose, the magnitude of effect was observed to be greater for the higher dose.

Nighttime sleep measured with polysomnography was not affected by the use of NUVIGIL.

Shift Work Disorder (SWD)

The effectiveness of NUVIGIL in improving wakefulness in patients with excessive sleepiness associated with SWD was demonstrated in a 12-week, multi-center, double-blind, placebo-controlled, parallel-group, clinical trial. A total of 254 patients with chronic SWD were randomized to receive NUVIGIL 150 mg/day or placebo. All patients met the ICSD criteria for chronic SWD [which are consistent with the American Psychiatric Association DSM-IV criteria for Circadian Rhythm Sleep Disorder: Shift Work Type]. These criteria include 1) either: a) a primary complaint of excessive sleepiness or insomnia which is temporally associated with a work period (usually night work) that occurs during the habitual sleep phase, or b) polysomnography and the MSLT demonstrate loss of a normal sleep-wake pattern (i.e., disturbed chronobiological rhythmicity); and 2) no other medical or mental disorder accounts for the symptoms, and 3) the symptoms do not meet criteria for any other sleep disorder producing insomnia or excessive sleepiness (e.g., time zone change [jet lag] syndrome).

It should be noted that not all patients with a complaint of sleepiness who are also engaged in shift work meet the criteria for the diagnosis of SWD. In the clinical trial, only patients who were symptomatic for at least 3 months were enrolled.

Enrolled patients were also required to work a minimum of 5 night shifts per month, have excessive sleepiness at the time of their night shifts (MSLT score ≤ 6 minutes), and have daytime insomnia documented by a daytime polysomnogram (PSG).

The primary measures of effectiveness were 1) sleep latency, as assessed by the Multiple Sleep Latency Test (MSLT) performed during a simulated night shift at the final visit, and 2) the change in the patient’s overall disease status, as measured by the Clinical Global Impression of Change (CGI-C) at the final visit. (SeeCLINICAL TRIALS, Narcolepsy andOSA sections above for description of these measures).

Patients treated with NUVIGIL showed a statistically significant prolongation in the time to sleep onset compared to placebo-treated patients, as measured by the nighttime MSLT at final visit [Table 1]. A statistically significant greater number of patients treated with NUVIGIL showed improvement in overall clinical condition as rated by the CGI-C scale at final visit [Table 2].

Daytime sleep measured with polysomnography was not affected by the use of NUVIGIL.

Table 1. Average Baseline Sleep Latency and Change from Baseline at Final Visit (MWT and MSLT in minutes)
Disorder | Measure | NUVIGIL 150 mg* |  | NUVIGIL 250 mg* |  | Placebo
 |  | Baseline | Change from Baseline | Baseline | Change from Baseline | Baseline | Change from Baseline
OSA I | MWT | 21.5 | 1.7 | 23.3 | 2.2 | 23.2 | -1.7
OSA II | MWT | 23.7 | 2.3 | - | - | 23.3 | -1.3
Narcolepsy | MWT | 12.1 | 1.3 | 9.5 | 2.6 | 12.5 | -1.9
SWD | MSLT | 2.3 | 3.1 | - | - | 2.4 | 0.4
*Significantly different than placebo for all trials (p<0.05)

Table 2. Clinical Global Impression of Change (CGI-C) (Percent of Patients Who Improved at Final Visit)
Disorder | NUVIGIL 150 mg* | NUVIGIL 250 mg* | Placebo
OSA I | 71% | 74% | 37%
OSA II | 71% | - | 53%
Narcolepsy | 69% | 73% | 33%
SWD | 79% | - | 59%
*Significantly different than placebo for all trials (p<0.05)

INDICATIONS AND USAGE

NUVIGIL is indicated to improve wakefulness in patients with excessive sleepiness associated with obstructive sleep apnea, narcolepsy and shift work disorder.

In OSA, NUVIGIL is indicated as an adjunct to standard treatment(s) for the underlying obstruction. If continuous positive airway pressure (CPAP) is the treatment of choice for a patient, a maximal effort to treat with CPAP for an adequate period of time should be made prior to initiating NUVIGIL. If NUVIGIL is used adjunctively with CPAP, the encouragement of and periodic assessment of CPAP compliance is necessary.

In all cases, careful attention to the diagnosis and treatment of the underlying sleep disorder(s) is of utmost importance. Prescribers should be aware that some patients may have more than one sleep disorder contributing to their excessive sleepiness.

The effectiveness of NUVIGIL in long-term use (greater than 12 weeks) has not been systematically evaluated in placebo-controlled trials. The physician who elects to prescribe NUVIGIL for an extended time in patients should periodically re-evaluate long-term usefulness for the individual patient.

CONTRAINDICATIONS

NUVIGIL is contraindicated in patients with known hypersensitivity to modafinil and armodafinil or its inactive ingredients.

WARNINGS

Serious Rash, including Stevens-Johnson Syndrome

Serious rash requiring hospitalization and discontinuation of treatment has been reported in adults in association with the use of modafinil and armodafinil and in children in association with the use of modafinil.

Armodafinil has not been studied in pediatric patients in any setting and is not approved for use in pediatric patients for any indication.

In clinical trials of modafinil (a racemic mixture of S and R enantiomers), the incidence of rash resulting in discontinuation was approximately 0.8% (13 per 1,585) in pediatric patients (age <17 years); these rashes included 1 case of possible Stevens-Johnson Syndrome (SJS) and 1 case of apparent multi-organ hypersensitivity reaction. Several of the cases were associated with fever and other abnormalities (e.g., vomiting, leukopenia). The median time to rash that resulted in discontinuation was 13 days. No such cases were observed among 380 pediatric patients who received placebo. No serious skin rashes have been reported in adult clinical trials (0 per 4,264) of modafinil. Rare cases of serious or life-threatening rash, including SJS, Toxic Epidermal Necrolysis (TEN), and Drug Rash with Eosinophilia and Systemic Symptoms (DRESS) have been reported in adults and children in worldwide post-marketing experience with modafinil. The reporting rate of TEN and SJS associated with modafinil use, which is generally accepted to be an underestimate due to underreporting, exceeds the background incidence rate. Estimates of the background incidence rate for these serious skin reactions in the general population range between 1 to 2 cases per million-person years.

No serious skin rashes have been reported in adult clinical trials (0 per 1,595) of armodafinil. However, cases of serious rash similar to those observed with modafinil including skin and mouth blistering have been reported in adults in postmarketing experience.

There are no factors that are known to predict the risk of occurrence or the severity of rash associated with armodafinil or modafinil. Nearly all cases of serious rash associated with these drugs occurred within 1 to 5 weeks after treatment initiation. However, isolated cases have been reported after prolonged treatment with modafinil (e.g., 3 months). Accordingly, duration of therapy cannot be relied upon as a means to predict the potential risk heralded by the first appearance of a rash.

Although benign rashes also occur with armodafinil, it is not possible to reliably predict which rashes will prove to be serious. Accordingly, armodafinil should ordinarily be discontinued at the first sign of rash, unless the rash is clearly not drug-related. Discontinuation of treatment may not prevent a rash from becoming life-threatening or permanently disabling or disfiguring.

Angioedema and Anaphylactoid Reactions

One serious case of angioedema and one case of hypersensitivity (with rash, dysphagia, and bronchospasm), were observed among 1,595 patients treated with armodafinil. Patients should be advised to discontinue therapy and immediately report to their physician any signs or symptoms suggesting angioedema or anaphylaxis (e.g., swelling of face, eyes, lips, tongue or larynx; difficulty in swallowing or breathing; hoarseness).

Multi-organ hypersensitivity reactions, including at least one fatality in postmarketing experience, have occurred in close temporal association (median time to detection 13 days: range 4-33) to the initiation of modafinil. A similar risk of multi-organ hypersensitivity reactions with armodafinil cannot be ruled out.

Although there have been a limited number of reports, multi-organ hypersensitivity reactions may result in hospitalization or be life-threatening. There are no factors that are known to predict the risk of occurrence or the severity of multi-organ hypersensitivity reactions associated with modafinil. Signs and symptoms of this disorder were diverse; however, patients typically, although not exclusively, presented with fever and rash associated with other organ system involvement. Other associated manifestations included myocarditis, hepatitis, liver function test abnormalities, hematological abnormalities (e.g., eosinophilia, leukopenia, thrombocytopenia), pruritus, and asthenia. Because multi-organ hypersensitivity is variable in its expression, other organ system symptoms and signs, not noted here, may occur.

If a multi-organ hypersensitivity reaction is suspected, NUVIGIL should be discontinued. Although there are no case reports to indicate cross-sensitivity with other drugs that produce this syndrome, the experience with drugs associated with multi-organ hypersensitivity would indicate this to be a possibility.

Persistent Sleepiness

Patients with abnormal levels of sleepiness who take NUVIGIL should be advised that their level of wakefulness may not return to normal. Patients with excessive sleepiness, including those taking NUVIGIL, should be frequently reassessed for their degree of sleepiness and, if appropriate, advised to avoid driving or any other potentially dangerous activity. Prescribers should also be aware that patients may not acknowledge sleepiness or drowsiness until directly questioned about drowsiness or sleepiness during specific activities.

Psychiatric Symptoms

Psychiatric adverse experiences have been reported in patients treated with modafinil. Modafinil and armodafinil (NUVIGIL) are very closely related. Therefore, the incidence and type of psychiatric symptoms associated with armodafinil are expected to be similar to the incidence and type of these events with modafinil.

Postmarketing adverse events associated with the use of modafinil have included mania, delusions, hallucinations, suicidal ideation and aggression, some resulting in hospitalization. Many, but not all, patients had a prior psychiatric history. One healthy male volunteer developed ideas of reference, paranoid delusions, and auditory hallucinations in association with multiple daily 600 mg doses of modafinil and sleep deprivation. There was no evidence of psychosis 36 hours after drug discontinuation.

In the controlled trial NUVIGIL database, anxiety, agitation, nervousness, and irritability were reasons for treatment discontinuation more often in patients on NUVIGIL compared to placebo (NUVIGIL 1.2% and placebo 0.3%). In the NUVIGIL controlled studies, depression was also a reason for treatment discontinuation more often in patients on NUVIGIL compared to placebo (NUVIGIL 0.6% and placebo 0.2%). Two cases of suicide ideation were observed in clinical trials. Caution should be exercised when NUVIGIL is given to patients with a history of psychosis, depression, or mania. If psychiatric symptoms develop in association with NUVIGIL administration, consider discontinuing NUVIGIL.

PRECAUTIONS

Diagnosis of Sleep Disorders

NUVIGIL should be used only in patients who have had a complete evaluation of their excessive sleepiness, and in whom a diagnosis of either narcolepsy, OSA, and/or SWD has been made in accordance with ICSD or DSM diagnostic criteria (SeeCLINICAL TRIALS). Such an evaluation usually consists of a complete history and physical examination, and it may be supplemented with testing in a laboratory setting. Some patients may have more than one sleep disorder contributing to their excessive sleepiness (e.g., OSA and SWD coincident in the same patient).

CPAP Use in Patients with OSA

In OSA, NUVIGIL is indicated as an adjunct to standard treatment(s) for the underlying obstruction. If continuous positive airway pressure (CPAP) is the treatment of choice for a patient, a maximal effort to treat with CPAP for an adequate period of time should be made prior to initiating NUVIGIL. If NUVIGIL is used adjunctively with CPAP, the encouragement of and periodic assessment of CPAP compliance is necessary. There was a slight trend for reduced CPAP use over time (mean reduction of 18 minutes for patients treated with NUVIGIL and a 6 minute reduction for placebo-treated patients from a mean baseline use of 6.9 hours per night) in NUVIGIL trials.

General

Although NUVIGIL has not been shown to produce functional impairment, any drug affecting the CNS may alter judgment, thinking or motor skills. Patients should be cautioned about operating an automobile or other hazardous machinery until they are reasonably certain that NUVIGIL therapy will not adversely affect their ability to engage in such activities.

Cardiovascular System

NUVIGIL has not been evaluated or used to any appreciable extent in patients with a recent history of myocardial infarction or unstable angina, and such patients should be treated with caution.

In clinical studies of PROVIGIL, signs and symptoms including chest pain, palpitations, dyspnea and transient ischemic T-wave changes on ECG were observed in three subjects in association with mitral valve prolapse or left ventricular hypertrophy. It is recommended that NUVIGIL tablets not be used in patients with a history of left ventricular hypertrophy or in patients with mitral valve prolapse who have experienced the mitral valve prolapse syndrome when previously receiving CNS stimulants. Signs of mitral valve prolapse syndrome include but are not limited to ischemic ECG changes, chest pain, or arrhythmia. If new onset of any of these symptoms occurs, consider cardiac evaluation.

Blood pressure monitoring in short-term (≤ 3 months) controlled trials showed only small average increases in mean systolic and diastolic blood pressure in patients receiving NUVIGIL as compared to placebo (1.2 to 4.3 mmHg in the various experimental groups). There was also a slightly greater proportion of patients on NUVIGIL requiring new or increased use of antihypertensive medications (2.9%) compared to patients on placebo (1.8%). Increased monitoring of blood pressure may be appropriate in patients on NUVIGIL.

Patients Using Steroidal Contraceptives

The effectiveness of steroidal contraceptives may be reduced when used with NUVIGIL and for one month after discontinuation of therapy (SeePRECAUTIONS, Drug Interactions). Alternative or concomitant methods of contraception are recommended for patients treated with NUVIGIL and for one month after discontinuation of NUVIGIL treatment.

Patients Using Cyclosporine

The blood levels of cyclosporine may be reduced when used with NUVIGIL (See PRECAUTIONS, Drug Interactions). Monitoring of circulating cyclosporine concentrations and appropriate dosage adjustment for cyclosporine should be considered when these drugs are used concomitantly.

Patients with Severe Hepatic Impairment

In patients with severe hepatic impairment, with or without cirrhosis (SeeCLINICAL PHARMACOLOGY), NUVIGIL should be administered at a reduced dose (SeeDOSAGE AND ADMINISTRATION).

Patients with Severe Renal Impairment

There is inadequate information to determine safety and efficacy of dosing in patients with severe renal impairment (For pharmacokinetics in renal impairment, seeCLINICAL PHARMACOLOGY.)

Elderly Patients

In elderly patients, elimination of armodafinil and its metabolites may be reduced as a consequence of aging. Therefore, consideration should be given to the use of lower doses in this population (SeeCLINICAL PHARMACOLOGYandDOSAGE AND ADMINISTRATION).

Information for Patients

Physicians are advised to discuss the following issues with patients for whom they prescribe NUVIGIL.

NUVIGIL is indicated for patients who have abnormal levels of sleepiness. NUVIGIL has been shown to improve, but not eliminate, this abnormal tendency to fall asleep. Therefore, patients should not alter their previous behavior with regard to potentially dangerous activities (e.g., driving, operating machinery) or other activities requiring appropriate levels of wakefulness, until and unless treatment with NUVIGIL has been shown to produce levels of wakefulness that permit such activities. Patients should be advised that NUVIGIL is not a replacement for sleep.

Patients should be informed that it may be critical that they continue to take their previously prescribed treatments (e.g., patients with OSA receiving CPAP should continue to do so).

Patients should be informed of the availability of a Medication Guide, and they should be instructed to read it prior to taking NUVIGIL. The complete text of the Medication Guide is provided at the end of this labeling.

Patients should be advised to contact their physician if they experience rash, depression, anxiety, or signs of psychosis or mania.

Pregnancy

Patients should be advised to notify their physician if they become pregnant or intend to become pregnant during therapy. Patients should be cautioned regarding the potential increased risk of pregnancy when using steroidal contraceptives (including depot or implantable contraceptives) with NUVIGIL and for one month after discontinuation of therapy (SeeCarcinogenesis, Mutagenesis, Impairment of Fertility andPregnancy).

Nursing

Patients should be advised to notify their physician if they are breastfeeding an infant.

Concomitant Medication

Patients should be advised to inform their physician if they are taking, or plan to take, any prescription or over-the-counter drugs, because of the potential for interactions between NUVIGIL and other drugs.

Alcohol

Patients should be advised that the use of NUVIGIL in combination with alcohol has not been studied. Patients should be advised that it is prudent to avoid alcohol while taking NUVIGIL.

Allergic Reactions

Patients should be advised to stop taking NUVIGIL and to notify their physician if they develop a rash, hives, mouth sores, blisters, peeling skin, trouble swallowing or breathing or a related allergic phenomenon.

Drug Interactions

Potential Interactions with Drugs That Inhibit, Induce, or Are Metabolized by Cytochrome P450 Isoenzymes and Other Hepatic Enzymes

Due to the partial involvement of CYP3A enzymes in the metabolic elimination of armodafinil, coadministration of potent inducers of CYP3A4/5 (e.g., carbamazepine, phenobarbital, rifampin) or inhibitors of CYP3A4/5 (e.g., ketoconazole, erythromycin) could alter the plasma levels of armodafinil.

The Potential of NUVIGIL to Alter the Metabolism of Other Drugs by Enzyme Induction or Inhibition

Drugs Metabolized by CYP1A2

In vitro data demonstrated that armodafinil shows a weak inductive response for CYP1A2 and possibly CYP3A activities in a concentration related manner and demonstrated that CYP2C19 activity is reversibly inhibited by armodafinil. However, the effect on CYP1A2 activity was not observed clinically in an interaction study performed with caffeine (See Pharmacokinetics, Drug-Drug Interactions).

Drugs Metabolized by CYP3A4/5 (e.g., cyclosporine, ethinyl estradiol, midazolam and triazolam)

Chronic administration of NUVIGIL resulted in moderate induction of CYP3A activity. Hence, the effectiveness of drugs that are substrates for CYP3A enzymes (e.g., cyclosporine, ethinyl estradiol, midazolam and triazolam) may be reduced after initiation of concurrent treatment with NUVIGIL. A 32% reduction in systemic exposure of oral midazolam was seen upon concomitant administration of armodafinil with midazolam. Dose adjustment may be required (See Pharmacokinetics, Drug-Drug Interactions). Such effects (reduced concentrations) were also seen upon concomitant administration of modafinil with cyclosporine, ethinyl estradiol, and triazolam.

Drugs Metabolized by CYP2C19 (e.g., omeprazole, diazepam, phenytoin, and propranolol)

Administration of NUVIGIL resulted in moderate inhibition of CYP2C19 activity. Hence, dosage reduction may be required for some drugs that are substrates for CYP2C19 (e.g., phenytoin, diazepam, and propranolol, omeprazole and clomipramine) when used concurrently with NUVIGIL. A 40% increase in exposure was seen upon concomitant administration of armodafinil with omeprazole. (SeePharmacokinetics, Drug-Drug Interactions).

Interactions with CNS Active Drugs

Data specific to armodafinil drug-drug interaction potential with CNS active drugs are not available. However, the following available drug-drug interaction information on modafinil should be applicable to armodafinil (SeeDESCRIPTIONand CLINICAL PHARMACOLOGY).

Concomitant administration of modafinil with methylphenidate, or dextroamphetamine produced no significant alterations on the pharmacokinetic profile of modafinil or either stimulant, even though the absorption of modafinil was delayed for approximately one hour.

Concomitant modafinil or clomipramine did not alter the PK profile of either drug; however, one incident of increased levels of clomipramine and its active metabolite desmethylclomipramine was reported in a patient with narcolepsy during treatment with modafinil.

Data specific to armodafinil or modafinil drug-drug interaction potential with Monoamine Oxidase (MAO) inhibitors are not available. Therefore, caution should be used when concomitantly administering MAO inhibitors and NUVIGIL.

Interactions with Other Drugs

Data specific to armodafinil drug-drug interaction potential for additional other drugs are not available. However, the following available drug-drug interaction information on modafinil should be applicable to armodafinil.

Warfarin

Concomitant administration of modafinil with warfarin did not produce significant changes in the pharmacokinetic profiles of R- and S-warfarin. However, since only a single dose of warfarin was tested in this study, a pharmacodynamic interaction cannot be ruled out. Therefore, more frequent monitoring of prothrombin times/INR should be considered whenever NUVIGIL is coadministered with warfarin.

Carcinogenesis, Mutagenesis, Impairment of Fertility

Carcinogenesis

Carcinogenicity studies have not been conducted with armodafinil alone. Carcinogenicity studies were conducted in which modafinil was administered in the diet to mice for 78 weeks and to rats for 104 weeks at doses of 6, 30, and 60 mg/kg/day. The highest dose studied represents 1.5 (mouse) or 3 (rat) times greater than the recommended adult human daily dose of modafinil (200 mg) on a mg/m^2 basis. There was no evidence of tumorigenesis associated with modafinil administration in these studies. However, since the mouse study used an inadequate high dose that was not representative of a maximum tolerated dose, a subsequent carcinogenicity study was conducted in the Tg.AC transgenic mouse. Doses evaluated in the Tg.AC assay were 125, 250, and 500 mg/kg/day, administered dermally. There was no evidence of tumorigenicity associated with modafinil administration; however, this dermal model may not adequately assess the carcinogenic potential of an orally administered drug.

Mutagenesis

Armodafinil was evaluated in an in vitro bacterial reverse mutation assay and in an in vitro mammalian chromosomal aberration assay in human lymphocytes. Armodafinil was negative in these assays, both in the absence and presence of metabolic activation. Modafinil demonstrated no evidence of mutagenic or clastogenic potential in a series of in vitro (i.e., bacterial reverse mutation assay, mouse lymphoma tk assay, chromosomal aberration assay in human lymphocytes, cell transformation assay in BALB/3T3 mouse embryo cells) assays in the absence or presence of metabolic activation, or in vivo (mouse bone marrow micronucleus) assays. Modafinil was also negative in the unscheduled DNA synthesis assay in rat hepatocytes.

Impairment of Fertility

A fertility and early embryonic development (to implantation) study was not conducted with armodafinil alone.

Oral administration of modafinil (doses of up to 480 mg/kg/day) to male and female rats prior to and throughout mating, and continuing in females through day 7 of gestation produced an increase in the time to mate at the highest dose; no effects were observed on other fertility or reproductive parameters. The no-effect dose of 240 mg/kg/day was associated with a plasma modafinil exposure (AUC) approximately equal to that in humans at the recommended dose of 200 mg.

Pregnancy

Pregnancy Category C

In studies conducted in rats (armodafinil, modafinil) and rabbits (modafinil), developmental toxicity was observed at clinically relevant exposures.

Oral administration of armodafinil (60, 200, or 600 mg/kg/day) to pregnant rats throughout the period of organogenesis resulted in increased incidences of fetal visceral and skeletal variations at the intermediate dose or greater and decreased fetal body weights at the highest dose. The no-effect dose for rat embryofetal developmental toxicity was associated with a plasma armodafinil exposure (AUC) approximately 0.03 times the AUC in humans at the maximum recommended daily dose of 250 mg.

Modafinil (50, 100, or 200 mg/kg/day) administered orally to pregnant rats throughout the period of organogenesis caused, in the absence of maternal toxicity, an increase in resorptions and an increased incidence of visceral and skeletal variations in the offspring at the highest dose. The higher no-effect dose for rat embryofetal developmental toxicity was associated with a plasma modafinil exposure approximately 0.5 times the AUC in humans at the recommended daily dose (RHD) of 200 mg. However, in a subsequent study of up to 480 mg/kg/day (plasma modafinil exposure approximately 2 times the AUC in humans at the RHD) no adverse effects on embryofetal development were observed.

Modafinil administered orally to pregnant rabbits throughout the period of organogenesis at doses of up to 100 mg/kg/day (plasma modafinil AUC approximately equal to the AUC in humans at the RHD) had no effect on embryofetal development; however, the doses used were too low to adequately assess the effects of modafinil on embryofetal development. In a subsequent developmental toxicity study evaluating doses of 45, 90, and 180 mg/kg/day in pregnant rabbits, the incidences of fetal structural alterations and embryofetal death were increased at the highest dose. The highest no-effect dose for developmental toxicity was associated with a plasma modafinil AUC approximately equal to the AUC in humans at the RHD.

Modafinil administration to rats throughout gestation and lactation at oral doses of up to 200 mg/kg/day resulted in decreased viability in the offspring at doses greater than 20 mg/kg/day (plasma modafinil AUC approximately 0.1 times the AUC in humans at the RHD). No effects on postnatal developmental and neurobehavioral parameters were observed in surviving offspring.

There are no adequate and well-controlled studies of either armodafinil or modafinil in pregnant women. Two cases of intrauterine growth retardation and one case of spontaneous abortion have been reported in association with armodafinil and modafinil. Although the pharmacology of armodafinil is not identical to that of the sympathomimetic amines, it does share some pharmacologic properties with this class.

Certain of these drugs have been associated with intrauterine growth retardation and spontaneous abortions. Whether the cases reported with armodafinil are drug-related is unknown.

Armodafinil or modafinil should be used during pregnancy only if the potential benefit justifies the potential risk to the fetus.

Pregnancy Registry: A pregnancy registry has been established to collect information on the pregnancy outcomes of women exposed to NUVIGIL. Healthcare providers are encouraged to register pregnant patients, or pregnant women may enroll themselves in the registry by calling 1-866-404-4106 (toll free).

Labor and Delivery

The effect of armodafinil on labor and delivery in humans has not been systematically investigated.

Nursing Mothers

It is not known whether armodafinil or its metabolites are excreted in human milk. Because many drugs are excreted in human milk, caution should be exercised when NUVIGIL tablets are administered to a nursing woman.

Pediatric Use

Safety and effectiveness of armodafinil use in individuals below 17 years of age have not been established. Serious rash has been seen in pediatric patients receiving modafinil (SeeWARNINGS, Serious Rash, including Stevens-Johnson Syndrome).

Geriatric Use

In elderly patients, elimination of armodafinil and its metabolites may be reduced as a consequence of aging. Therefore, consideration should be given to the use of lower doses in this population (See CLINICAL PHARMACOLOGY and PRECAUTIONS).

ADVERSE REACTIONS

Armodafinil has been evaluated for safety in over 1100 patients with excessive sleepiness associated with primary disorders of sleep and wakefulness. In clinical trials, NUVIGIL has been found to be generally well tolerated and most adverse experiences were mild to moderate.

In the placebo-controlled clinical studies, the most commonly observed adverse events (≥ 5%) associated with the use of NUVIGIL occurring more frequently than in the placebo-treated patients were headache, nausea, dizziness, and insomnia. The adverse event profile was similar across the studies.

In the placebo-controlled clinical trials, 44 of the 645 patients (7%) who received NUVIGIL discontinued due to an adverse experience compared to 16 of the 445 (4%) of patients that received placebo. The most frequent reason for discontinuation was headache (1%).

Incidence in Controlled Trials

The following table (Table 3) presents the adverse experiences that occurred at a rate of 1% or more and were more frequent in patients treated with NUVIGIL than in placebo group patients in the placebo-controlled clinical trials.

The prescriber should be aware that the figures provided below cannot be used to predict the frequency of adverse experiences in the course of usual medical practice, where patient characteristics and other factors may differ from those occurring during clinical studies. Similarly, the cited frequencies cannot be directly compared with figures obtained from other clinical investigations involving different treatments, uses, or investigators. Review of these frequencies, however, provides prescribers with a basis to estimate the relative contribution of drug and non-drug factors to the incidence of adverse events in the population studied.

Table 3. Incidence > 1% (In Percent) Of Treatment-Emergent Adverse Experiences In Parallel-Group, Placebo-Controlled Clinical Trialsª In OSA, Narcolepsy and SWD With NUVIGIL (150 mg and 250 mg)

System Organ Class MedDRA preferred term | NUVIGIL (Percent, N=645) | Placebo (Percent, N=445)
Cardiac Disorders
Palpitations | 2 | 1
Gastrointestinal Disorders
Nausea | 7 | 3
Diarrhea | 4 | 2
Dry Mouth | 4 | 1
Dyspepsia | 2 | 0
Abdominal Pain Upper | 2 | 1
Constipation | 1 | 0
Vomiting | 1 | 0
Loose Stools | 1 | 0
General Disorders And Administration Site Conditions
Fatigue | 2 | 1
Thirst | 1 | 0
Influenza-Like Illness | 1 | 0
Pain | 1 | 0
Pyrexia | 1 | 0
Immune System Disorders
Seasonal Allergy | 1 | 0
Investigations
Gamma-Glutamyltransferase Increased | 1 | 0
Heart Rate Increased | 1 | 0
Metabolism And Nutrition Disorders
Anorexia | 1 | 0
Decreased Appetite | 1 | 0
Nervous System Disorders
Headache | 17 | 9
Dizziness | 5 | 2
Disturbance In Attention | 1 | 0
Tremor | 1 | 0
Migraine | 1 | 0
Paresthesia | 1 | 0
Psychiatric Disorders
Insomnia | 5 | 1
Anxiety | 4 | 1
Depression | 2 | 0
Agitation | 1 | 0
Nervousness | 1 | 0
Depressed Mood | 1 | 0
Renal And Urinary Disorders
Polyuria | 1 | 0
Respiratory, Thoracic And Mediastinal Disorders
Dyspnea | 1 | 0
Skin And Subcutaneous Tissue Disorders
Rash | 2 | 0
Contact Dermatitis | 1 | 0
Hyperhydrosis | 1 | 0
ª Four double-blind, placebo-controlled clinical studies in SWD, OSA, and narcolepsy; incidence is rounded to the nearest whole percent. Included are only those events for which NUVIGIL incidence is greater than that of placebo.

Dose Dependency of Adverse Events

In the placebo-controlled clinical trials which compared doses of 150 mg/day and 250 mg/day of NUVIGIL and placebo, the only adverse events that appeared to be dose-related were headache, rash, depression, dry mouth, insomnia, and nausea.

Table 4. Incidence (In Percent) Of Dose-Dependent , Treatment-Emergent Adverse Experiences By Dose and By Treatment In Parallel-Group, Placebo-Controlled Clinical Trialsa In OSA, Narcolepsy and SWD With NUVIGIL (150 mg and 250 mg)

System Organ Class MedDRA preferred term | NUVIGIL 250 mg (Percent, N=198) | NUVIGIL 150 mg (Percent, N=447) | NUVIGIL Combined (Percent, N=645) | Placebo (Percent, N=445)
Gastrointestinal Disorders
Nausea | 9 | 6 | 7 | 3
Dry Mouth | 7 | 2 | 4 | <1
Nervous System Disorders
Headache | 23 | 14 | 17 | 9
Psychiatric Disorders
Insomnia | 6 | 4 | 5 | 1
Depression | 3 | 1 | 2 | <1
Skin And Subcutaneous Tissue Disorders
Rash | 4 | 1 | 2 | <1
ª Four double-blind, placebo-controlled clinical studies in SWD, OSA, and narcolepsy.

Vital Sign Changes

There were small, but consistent, increases in average values for mean systolic and diastolic blood pressure in controlled trials (SeePRECAUTIONS). There was a small, but consistent, average increase in pulse rate over placebo in controlled trials. This increase varied from 0.9 to 3.5 BPM.

Laboratory Changes

Clinical chemistry, hematology, and urinalysis parameters were monitored in the studies. Mean plasma levels of gamma glutamyltransferase (GGT) and alkaline phosphatase (AP) were found to be higher following administration of NUVIGIL, but not placebo. Few subjects, however, had GGT or AP elevations outside of the normal range. No differences were apparent in alanine aminotransferase, aspartate aminotransferase, total protein, albumin, or total bilirubin, although there were rare cases of isolated elevations of AST and/or ALT. A single case of mild pancytopenia was observed after 35-days of treatment and resolved with drug discontinuation. A small mean decrease from baseline in serum uric acid compared to placebo was seen in clinical trials. The clinical significance of this finding is unknown.

ECG Changes

No pattern of ECG abnormalities could be attributed to NUVIGIL administration in placebo-controlled clinical trials.

DRUG ABUSE AND DEPENDENCE

Controlled Substance Class

Armodafinil (NUVIGIL) is a Schedule IV controlled substance.

Abuse Potential and Dependence

Although the abuse potential of armodafinil has not been specifically studied, its abuse potential is likely to be similar to that of modafinil (PROVIGIL). In humans, modafinil produces psychoactive and euphoric effects, alterations in mood, perception, thinking and feelings typical of other CNS stimulants. In in vitro binding studies, modafinil binds to the dopamine reuptake site and causes an increase in extracellular dopamine, but no increase in dopamine release. Modafinil is reinforcing, as evidenced by its self-administration in monkeys previously trained to self-administer cocaine. In some studies, modafinil was also partially discriminated as stimulant-like. Physicians should follow patients closely, especially those with a history of drug and/or stimulant (e.g., methylphenidate, amphetamine, or cocaine) abuse. Patients should be observed for signs of misuse or abuse (e.g., incrementation of doses or drug-seeking behavior).

The abuse potential of modafinil (200, 400, and 800 mg) was assessed relative to methylphenidate (45 and 90 mg) in an inpatient study in individuals experienced with drugs of abuse. Results from this clinical study demonstrated that modafinil produced psychoactive and euphoric effects and feelings consistent with other scheduled CNS stimulants (methylphenidate).

OVERDOSAGE

Human Experience

There were no overdoses reported in the NUVIGIL clinical studies. Symptoms of NUVIGIL overdose are likely to be similar to those of modafinil. Overdose in modafinil clinical trials included excitation or agitation, insomnia, and slight or moderate elevations in hemodynamic parameters. From post-marketing experience with modafinil, there have been no reports of fatal overdoses involving modafinil alone (doses up to 12 grams). Overdoses involving multiple drugs, including modafinil, have resulted in fatal outcomes. Symptoms most often accompanying modafinil overdose, alone or in combination with other drugs have included; insomnia; central nervous system symptoms such as restlessness, disorientation, confusion, excitation and hallucination; digestive changes such as nausea and diarrhea; and cardiovascular changes such as tachycardia, bradycardia, hypertension and chest pain.

Overdose Management

No specific antidote exists for the toxic effects of a NUVIGIL overdose. Such overdoses should be managed with primarily supportive care, including cardiovascular monitoring. If there are no contraindications, induced emesis or gastric lavage should be considered. There are no data to suggest the utility of dialysis or urinary acidification or alkalinization in enhancing drug elimination. The physician should consider contacting a poison-control center for advice in the treatment of any overdose.

DOSAGE AND ADMINISTRATION

Obstructive Sleep Apnea (OSA) and Narcolepsy

The recommended dose of NUVIGIL for patients with OSA or narcolepsy is 150 mg or 250 mg given as a single dose in the morning. In patients with OSA, doses up to 250 mg/day, given as a single dose, have been well tolerated, but there is no consistent evidence that this dose confers additional benefit beyond that of the 150 mg/day dose (See CLINICAL PHARMACOLOGY andCLINICAL TRIALS).

Shift Work Sleep Disorder (SWD)

The recommended dose of NUVIGIL for patients with SWD is 150 mg given daily approximately 1 hour prior to the start of their work shift.

Dosage adjustment should be considered for concomitant medications that are substrates for CYP3A4/5, such as steroidal contraceptives, triazolam, and cyclosporine (See PRECAUTIONS, Drug Interactions).

Drugs that are largely eliminated via CYP2C19 metabolism, such as diazepam, propranolol, and phenytoin may have prolonged elimination upon coadministration with NUVIGIL and may require dosage reduction and monitoring for toxicity (See PRECAUTIONS, Drug Interactions).

In patients with severe hepatic impairment, NUVIGIL should be administered at a reduced dose (See CLINICAL PHARMACOLOGYandPRECAUTIONS).

There is inadequate information to determine safety and efficacy of dosing in patients with severe renal impairment (SeeCLINICAL PHARMACOLOGYandPRECAUTIONS).

In elderly patients, elimination of armodafinil and its metabolites may be reduced as a consequence of aging. Therefore, consideration should be given to the use of lower doses in this population (See CLINICAL PHARMACOLOGY andPRECAUTIONS).

HOW SUPPLIED

NUVIGIL® (armodafinil) Tablets [C-IV]

150 mg:Each oval, white uncoated tablet is debossed with "C" on one side and "215" on the other.

NDC 16590-345-30 - Bottles of 30

250 mg: Each oval, white uncoated tablet is debossed with "C" on one side and "225" on the other.

NDC 16590-394-30 - Bottles of 30

Store at 20° - 25° C (68° - 77° F).

Distributed by:

Cephalon, Inc.

Frazer, PA 19355

U.S. Patent Nos. RE37,516; 7,132,570; 7,297,346

NUVIGIL is a trademark of Cephalon, Inc. or its affiliates.

© 2007-2010 Cephalon, Inc. All rights reserved.

October 2010

NUV-006

Relabeling and Repackaging by:
STAT Rx USA LLC
Gainesville, GA 30501

Medication Guide

NUVIGIL (nu-vij-el) C-IV

(armodafinil)

Tablets

Read the Medication Guide that comes with NUVIGIL before you start taking it and each time you get a refill. There may be new information. This Medication Guide does not take the place of talking with your doctor about your condition or treatment.

What is the most important information I should know about NUVIGIL?

NUVIGIL may cause serious side effects including a serious rash or a serious allergic reaction that may affect parts of your body such as your liver or blood cells. Any of these may need to be treated in a hospital and may be life-threatening.

Stop taking NUVIGIL and call your doctor right away or get emergency help if you have any of these symptoms:

-
  - skin rash, hives, sores in your mouth, or your skin blisters and peels
  - swelling of your face, eyes, lips, tongue, or throat
  - trouble swallowing or breathing
  - fever, shortness of breath, swelling of the legs, yellowing of the skin or whites of the eyes, or dark urine.

If you have a severe rash with NUVIGIL, stopping the medicine may not keep the rash from becoming life-threatening or causing you to be permanently disabled or disfigured.

NUVIGIL is not approved for use in children for any medical condition.

It is not known if NUVIGIL is safe or if it works in children under the age of 17.

What is NUVIGIL?

NUVIGIL is a prescription medicine used to improve wakefulness in adults who are very sleepy due to one of the following diagnosed sleep disorders:

- narcolepsy
- obstructive sleep apnea (OSA). NUVIGIL is used with other medical treatments for this sleep disorder. NUVIGIL does not take the place of using your CPAP machine or other treatments that your doctor has prescribed for this condition. It is important that you continue to use these treatments as prescribed by your doctor.
- shift work disorder (SWD)

NUVIGIL will not cure these sleep disorders. NUVIGIL may help the sleepiness caused by these conditions, but it may not stop all your sleepiness. NUVIGIL does not take the place of getting enough sleep. Follow your doctor's advice about good sleep habits and using other treatments.

Who should not take NUVIGIL?

Do not take NUVIGIL if you:

- are allergic to any of its ingredients. See the end of this Medication Guide for a complete list of ingredients in NUVIGIL.
- have had a rash or allergic reaction to either armodafinil (NUVIGIL) or modafinil (PROVIGIL®). These medicines are very similar.

What should I tell my doctor before taking NUVIGIL?

Tell your doctor about all of your medical conditions including, if you:

- have a history of mental health problems, including psychosis
- have heart problems or had a heart attack
- have high blood pressure. Your blood pressure may need to be checked more often while taking NUVIGIL.
- have liver or kidney problems
- have a history of drug or alcohol abuse or addiction
- are pregnant or planning to become pregnant. It is not known if NUVIGIL will harm your unborn baby.
  Pregnancy Registry: There is a registry for women who become pregnant during treatment with NUVIGIL. The purpose of this registry is to collect information about the safety of NUVIGIL during pregnancy. Contact the registry as soon as you learn that you are pregnant, or ask your doctor to contact the registry for you. You or your doctor can get information and enroll you in the registry by calling 1-866-404-4106.
- are breastfeeding. It is not known if NUVIGIL passes into your milk. Talk to your doctor about the best way to feed your baby if you take NUVIGIL.

Tell your doctor about all the medicines you take, including prescription and non-prescription medicines, vitamins, and herbal supplements. NUVIGIL and many other medicines can interact with each other, sometimes causing side effects. NUVIGIL may affect the way other medicines work, and other medicines may affect how NUVIGIL works. Your dose of NUVIGIL or certain other medicines may need to be changed.

Especially, tell your doctor if you use or take:

- a hormonal birth control method, such as birth control pills, shots, implants, patches, vaginal rings, and intrauterine devices (IUDs). Hormonal birth control methods may not work while you take NUVIGIL. Women who use one of these methods of birth control may have a higher chance for getting pregnant while taking NUVIGIL, and for one month after stopping NUVIGIL. Talk to your doctor about birth control choices that are right for you while taking NUVIGIL.

Know the medicines you take. Keep a list of them and show it to your doctor and pharmacist when you get a new medicine. Your doctor or pharmacist will tell you if it is safe to take NUVIGIL and other medicines together. Do not start any new medicines with NUVIGIL unless your doctor has told you it is okay.

How should I take NUVIGIL?

- Take NUVIGIL exactly as prescribed by your doctor. Your doctor will prescribe the dose of NUVIGIL that is right for you. Do not change your dose of NUVIGIL without talking to your doctor.
- Your doctor will tell you the right time of day to take NUVIGIL.
- People with narcolepsy or OSA usually take NUVIGIL one time each day in the morning.
- People with SWD usually take NUVIGIL about 1 hour before their work shift.
  - Do not change the time of day you take NUVIGIL unless you have talked to your doctor. If you take NUVIGIL too close to your bedtime, you may find it harder to go to sleep.
  - You can take NUVIGIL with or without food.
- If you take more than your prescribed dose or if you take an overdose of NUVIGIL, call your doctor or poison control center right away.

Symptoms of an overdose of NUVIGIL may include:

- Trouble sleeping
- Restlessness
- Confusion
- Feeling disoriented
- Feeling excited
- Hearing, seeing, feeling, or sensing things that are not really there (hallucinations)
- Nausea and diarrhea
- A fast or slow heartbeat
- Chest pain
- Increased blood pressure

What should I avoid while taking NUVIGIL?

- Do not drive a car or do other dangerous activities until you know how NUVIGIL affects you. People with sleep disorders should always be careful about doing things that could be dangerous. Do not change your daily habits until your doctor tells you it is okay.
- You should avoid drinking alcohol. It is not known how drinking alcohol will affect you when taking NUVIGIL.

What are possible side effects of NUVIGIL?

NUVIGIL may cause serious side effects. Stop taking NUVIGIL and call your doctor right away or get emergency help if you get any of the following:

- a serious rash or serious allergic reaction. (See “What is the most important information I should know about NUVIGIL?”)
- mental (psychiatric) symptoms, including:
  - depression
  - feeling anxious
  - hearing, seeing, feeling, or sensing things that are not really there (hallucinations)
  - an extreme increase in activity and talking (mania)
  - thoughts of suicide
  - aggressive behavior
  - other mental problems
- symptoms of a heart problem, including chest pain, abnormal heart beats, and trouble breathing.

Common side effects that can happen in anyone who takes NUVIGIL include:

- headache
- nausea
- dizziness
- trouble sleeping

Tell your doctor if you get any side effect that bothers you or that does not go away while taking NUVIGIL.

These are not all the side effects of NUVIGIL. For more information, ask your doctor or pharmacist.

Some effects of NUVIGIL on the brain are the same as other medicines called “stimulants”. These effects may lead to abuse or dependence on NUVIGIL.

Call your doctor for medical advice about side effects. You may report side effects to FDA at 1-800-FDA-1088.

How should I store NUVIGIL?

- Store NUVIGIL at room temperature between 68° and 77° F (20° and 25° C).
- Keep NUVIGIL and all medicines out of the reach of children.

General information about NUVIGIL

Medicines are sometimes prescribed for purposes other than those listed in a Medication Guide. Do not use NUVIGIL for a condition for which it was not prescribed. Do not give NUVIGIL to other people, even if they have the same symptoms you have. It may harm them and it is against the law.

This Medication Guide summarizes the most important information about NUVIGIL. If you would like more information, talk with your doctor. You can ask your doctor or pharmacist for information about NUVIGIL that is written for health professionals. For more information, call 1-800-896-5855, or go to www.NUVIGIL.com.

What are the ingredients in NUVIGIL?

Active Ingredient: armodafinil

Inactive Ingredients: lactose monohydrate, microcrystalline cellulose, pregelatinized starch, croscarmellose sodium, povidone, and magnesium stearate.

Distributed by:

Cephalon, Inc.

Frazer, PA 19355

NUVMG – 001

Revised October 2010

This Medication Guide has been approved by the U.S. Food and Drug Administration.

© 2007 - 2010 Cephalon, Inc. All rights reserved.

Relabeling and Repackaging by:
STAT Rx USA LLC
Gainesville, GA 30501